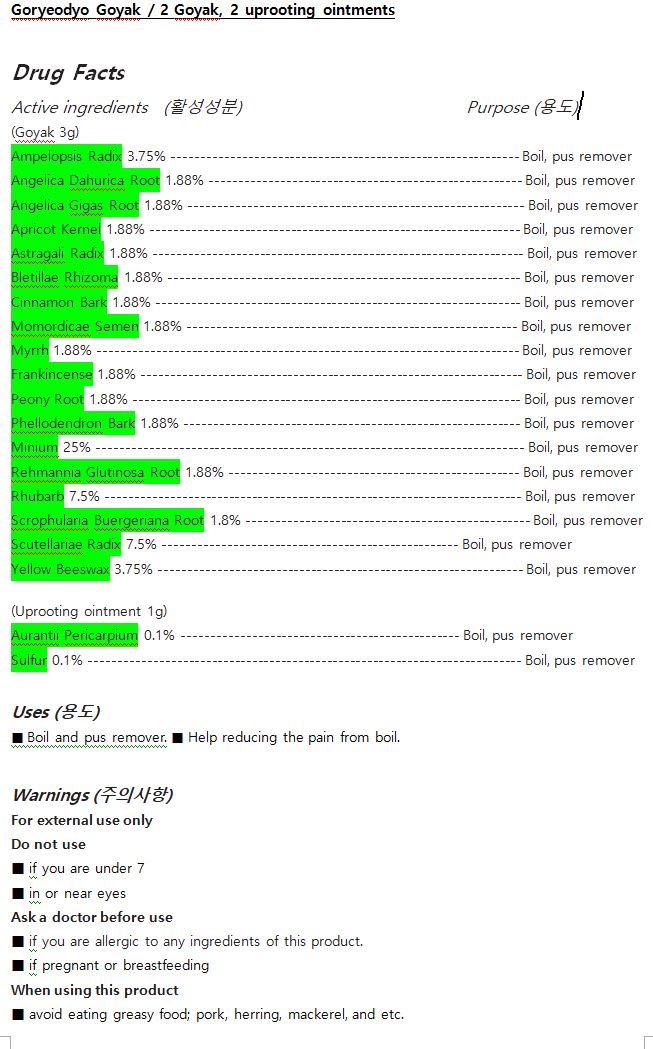 DRUG LABEL: Goryeodyo Goyak
NDC: 72850-0003 | Form: OINTMENT
Manufacturer: Chunwoo Pharmaceutical Co., Ltd.
Category: otc | Type: HUMAN OTC DRUG LABEL
Date: 20190320

ACTIVE INGREDIENTS: SCROPHULARIA BUERGERIANA ROOT 1.8 g/100 g; SCUTELLARIA BAICALENSIS ROOT 7.5 g/100 g; AMPELOPSIS JAPONICA TUBER 3.75 g/100 g; ANGELICA GIGAS ROOT OIL 1.88 g/100 g; RHUBARB 7.5 g/100 g; ASTRAGALUS PROPINQUUS ROOT 1.88 g/100 g; BLETILLA STRIATA TUBER 1.88 g/100 g; REHMANNIA GLUTINOSA ROOT 1.88 g/100 g; CINNAMON BARK OIL 1.88 g/100 g; FRANKINCENSE 1.88 g/100 g; MOMORDICA COCHINCHINENSIS SEED 1.88 g/100 g; PAEONIA LACTIFLORA ROOT 1.88 g/100 g; PHELLODENDRON CHINENSIS BARK 1.88 g/100 g; MYRRH 1.88 g/100 g; LEAD TETROXIDE 25 g/100 g; SULFUR 0.1 g/100 g; APRICOT KERNEL OIL 1.88 g/100 g; ANGELICA DAHURICA ROOT 1.88 g/100 g; YELLOW WAX 3.75 g/100 g; CITRUS AURANTIUM FRUIT RIND 0.1 g/100 g
INACTIVE INGREDIENTS: MENTHOL; CAMPHOR, (-)-

Drug Facts

ACTIVE INGREDIENT

Ampelopsis Radix 3.75% ------------------------------------------------------------ Boil, pus remover

Angelica Dahurica Root 1.88% ------------------------------------------------------ Boil, pus remover

Angelica Gigas Root 1.88% ---------------------------------------------------------- Boil, pus remover

Apricot Kernel 1.88% ---------------------------------------------------------------- Boil, pus remover

Astragali Radix 1.88% ---------------------------------------------------------------- Boil, pus remover

Bletillae Rhizoma 1.88% ------------------------------------------------------------- Boil, pus remover

Cinnamon Bark 1.88% --------------------------------------------------------------- Boil, pus remover

Momordicae Semen 1.88% --------------------------------------------------------- Boil, pus remover

Myrrh 1.88% ------------------------------------------------------------------------- Boil, pus remover

Frankincense 1.88% ------------------------------------------------------------------ Boil, pus remover

Peony Root 1.88% ------------------------------------------------------------------- Boil, pus remover

Phellodendron Bark 1.88% ---------------------------------------------------------- Boil, pus remover

Minium 25% -------------------------------------------------------------------------- Boil, pus remover

Rehmannia Glutinosa Root 1.88% -------------------------------------------------- Boil, pus remover

Rhubarb 7.5% ------------------------------------------------------------------------ Boil, pus remover

Scrophularia Buergeriana Root 1.8% ------------------------------------------------- Boil, pus remover

Scutellariae Radix 7.5% --------------------------------------------------- Boil, pus remover

Yellow Beeswax 3.75% --------------------------------------------------------------- Boil, pus remover

(Uprooting ointment 1g)

Aurantii Pericarpium 0.1% ------------------------------------------------ Boil, pus remover

Sulfur 0.1% --------------------------------------------------------------------------- Boil, pus remover

INACTIVE INGREDIENT

-Goyak

Camphor, Honey, Menthol, Menthyl Salicylate, Rice Oil

-Uprooting Ointment

Honey, Medical Soap, Rice Oil, Sucrose

PURPOSE

■ Boil and pus remover. ■ Help reducing the pain from a boil

keep out of reach of the children

INDICATIONS AND USAGE

■ when applying the plaster, melt the dark brown plaster with hand heat and knead it twice as big as the affected area. (If you are in cold place, put it on oil paper and melt it with match, candle and etc. for 5 to 10 seconds to help it stick well.)

■ before festering, attach the plaster only to cover the affected area.

■ when a pus or a boil is festering, insert an uprooting ointment into the area and attach the plaster on it.

■ Change to a new plaster after a day or two while symptom persists.

WARNINGS

For external use only
Do not use

■ if you are under 7

■ in or near eyes

Ask a doctor before use

■ if you are allergic to any ingredients of this product.

■ if pregnant or breastfeeding

When using this product

■ avoid eating greasy food; pork, herring, mackerel, and etc.

Stop use and ask a doctor if

■ rash, itching or excessive skin irritation develops

■ symptoms persist for more than 7 days or clear up and occur again within a few days

DOSAGE AND ADMINISTRATION

for external use only